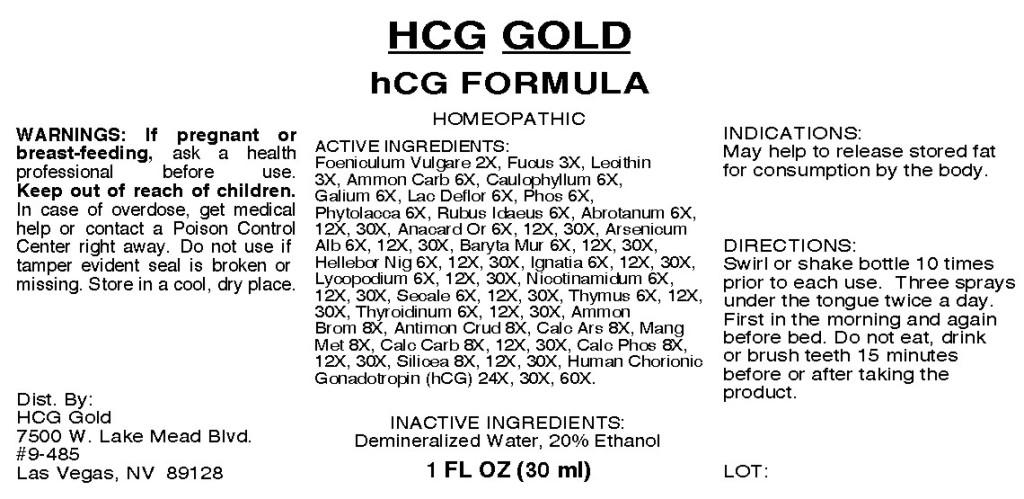 DRUG LABEL: hCG Formula
NDC: 57520-0609 | Form: SPRAY
Manufacturer: Apotheca Company
Category: homeopathic | Type: HUMAN OTC DRUG LABEL
Date: 20110208

ACTIVE INGREDIENTS: FENNEL SEED 2 [hp_X]/1 mL; FUCUS VESICULOSUS 3 [hp_X]/1 mL; LECITHIN, SOYBEAN 3 [hp_X]/1 mL; AMMONIUM CARBONATE 6 [hp_X]/1 mL; CAULOPHYLLUM THALICTROIDES ROOT 6 [hp_X]/1 mL; GALIUM APARINE 6 [hp_X]/1 mL; SKIM MILK 6 [hp_X]/1 mL; PHOSPHORUS 6 [hp_X]/1 mL; PHYTOLACCA AMERICANA ROOT 6 [hp_X]/1 mL; RUBUS IDAEUS LEAF 6 [hp_X]/1 mL; ARTEMISIA ABROTANUM FLOWERING TOP 30 [hp_X]/1 mL; SEMECARPUS ANACARDIUM JUICE 30 [hp_X]/1 mL; ARSENIC TRIOXIDE 30 [hp_X]/1 mL; BARIUM CHLORIDE DIHYDRATE 30 [hp_X]/1 mL; HELLEBORUS NIGER ROOT 30 [hp_X]/1 mL; STRYCHNOS IGNATII SEED 30 [hp_X]/1 mL; LYCOPODIUM CLAVATUM SPORE 30 [hp_X]/1 mL; NIACINAMIDE 30 [hp_X]/1 mL; CLAVICEPS PURPUREA SCLEROTIUM 30 [hp_X]/1 mL; SUS SCROFA THYMUS 30 [hp_X]/1 mL; SUS SCROFA THYROID 30 [hp_X]/1 mL; AMMONIUM BROMIDE 8 [hp_X]/1 mL; ANTIMONY TRISULFIDE 8 [hp_X]/1 mL; MANGANESE 8 [hp_X]/1 mL; OYSTER SHELL CALCIUM CARBONATE, CRUDE 30 [hp_X]/1 mL; TRIBASIC CALCIUM PHOSPHATE 30 [hp_X]/1 mL; SILICON DIOXIDE 30 [hp_X]/1 mL; HUMAN CHORIONIC GONADOTROPIN 60 [hp_X]/1 mL; CALCIUM ARSENATE 8 [hp_X]/1 mL
INACTIVE INGREDIENTS: WATER; ALCOHOL

hCG Formula

ACTIVE INGREDIENT

ACTIVE INGREDIENTS: Foeniculum vulgare 2X, Fucus vesiculosus 3X, Lecithin 3X, Ammonium carbonicum 6X, Caulophyllum thalictroides 6X, Galium aparine 6X, Lac defloratum 6X, Phosphorus 6X, Phytolacca decandra 6X, Rubus idaeus 6X, Abrotanum 6X, 12X, 30X, Anacardium orientale 6X, 12X, 30X, Arsenicum album 6X, 12X, 30X, Baryta muriatica 6X, 12X, 30X, Helleborus niger 6X, 12X, 30X, Ignatia amara 6X, 15X, 30X, Lycopodium clavatum 6X, 12X, 30X, Nicotinamidum 6X, 12X, 30X, Secale cornutum 6X, 12X, 30X, Thymus 6X, 12X, 30X, Thyroidinum 6X, 12X, 30X, Ammonium bromatum 8X, Antimonium crudum 8X, Calcarea arsenicica 8X, Manganum metallicum 8X, Calcarea carbonica 8X, 12X, 30X, Calcarea phosphorica 8X, 12X, 30X, Silicea 8X, 12X, 30X, Human chorionic gonadotropin 24X, 30X, 60X.

PURPOSE

INDICATIONS: May help to release stored fat for consumption by the body.

WARNINGS

WARNINGS: If pregnant or breast-feeding, ask a health professional before use.

Keep out of reach of children. In case of overdose, get medical help or contact a Poison Control Center right away.

Do not use if tamper evident seal is broken or missing. Store in a cool, dry place.

DOSAGE AND ADMINISTRATION

DIRECTIONS: Swirl or shake bottle 10 times prior to each use. Three sprays under the tongue twice a day. First in the morning and again before bed. Do not eat, drink or brush teeth 15 minutes before or after taking the product.

INACTIVE INGREDIENTS: Demineralized water, 20% Ethanol.

KEEP OUT OF REACH OF CHILDREN. In case of overdose, get medical help or contact a Poison Control Center right away.

INDICATIONS AND USAGE

INDICATIONS: May help to release stored fat for consumption by the body.

QUESTIONS

Dist. By:

HCG Gold

7500 W. Lake Mead Blvd.

#9-485

Las Vegas, NV 89128

PACKAGE LABEL

HCG GOLD

hCG FORMULA

HOMEOPATHIC

1 FL OZ (30 ml)